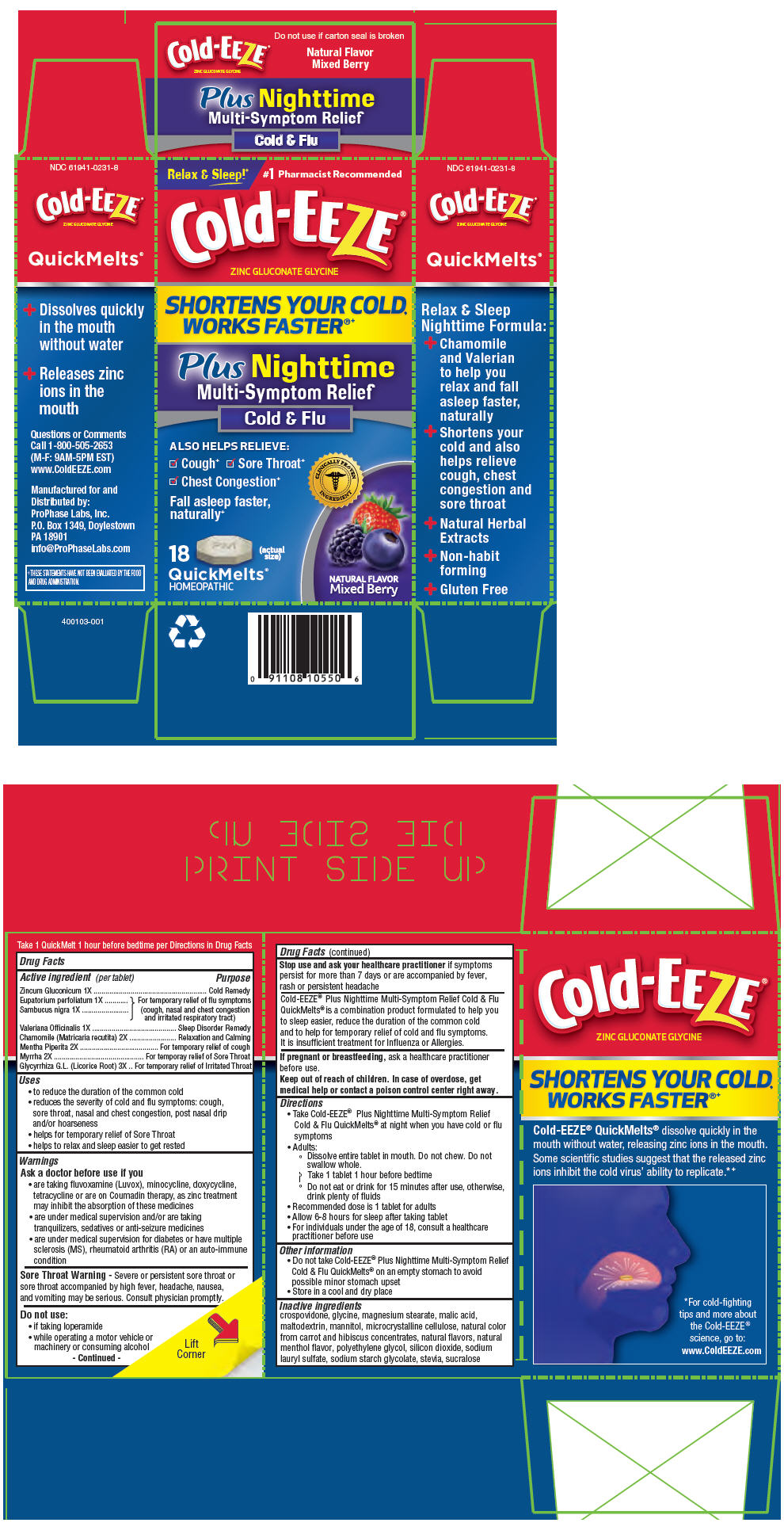 DRUG LABEL: Cold-EEZE 
NDC: 61941-0231 | Form: TABLET, ORALLY DISINTEGRATING
Manufacturer: ProPhase Labs, Inc.
Category: homeopathic | Type: HUMAN OTC DRUG LABEL
Date: 20160725

ACTIVE INGREDIENTS: Zinc Gluconate 1 [hp_X]/1 1; Eupatorium Perfoliatum Flowering Top 1 [hp_X]/1 1; Sambucus Nigra Flower 1 [hp_X]/1 1; Valerian 1 [hp_X]/1 1; Chamomile 2 [hp_X]/1 1; Mentha Piperita 2 [hp_X]/1 1; Myrrh 2 [hp_X]/1 1; Glycyrrhiza Glabra Leaf 3 [hp_X]/1 1
INACTIVE INGREDIENTS: CROSPOVIDONE (15 MPA.S AT 5%); GLYCINE; MAGNESIUM STEARATE; MALIC ACID; MALTODEXTRIN; MANNITOL; MICROCRYSTALLINE CELLULOSE; MENTHOL, UNSPECIFIED FORM; POLYETHYLENE GLYCOL, UNSPECIFIED; SILICON DIOXIDE; SODIUM LAURYL SULFATE; SODIUM STARCH GLYCOLATE TYPE A POTATO; STEVIA REBAUDIUNA LEAF; SUCRALOSE

Cold-EEZE®
Plus Nighttime Multi-Symptom Relief

Drug Facts

ACTIVE INGREDIENT

Active ingredient (per tablet) | Purpose
Zincum Gluconicum 1X | Cold Remedy
Eupatorium perfoliatum 1X | For temporary relief of flu symptoms
Sambucus nigra 1X | (cough, nasal and chest congestion and irritated respiratory tract)
Valeriana Officinalis 1X | Sleep Disorder Remedy
Chamomile (Matricaria recutita) 2X | Relaxation and Calming
Mentha Piperita 2X | For temporary relief of cough
Myrrha 2X | For temporay relief of Sore Throat
Glycyrrhiza G.L. (Licorice Root) 3X | For temporary relief of Irritated Throat

Uses

- to reduce the duration of the common cold
- reduces the severity of cold and flu symptoms: cough, sore throat, nasal and chest congestion, post nasal drip and/or hoarseness
- helps for temporary relief of Sore Throat
- helps to relax and sleep easier to get rested

Warnings

Ask a doctor before use if you

- are taking fluvoxamine (Luvox), minocycline, doxycycline, tetracycline or are on Coumadin therapy, as zinc treatment may inhibit the absorption of these medicines
- are under medical supervision and/or are taking tranquilizers, sedatives or anti-seizure medicines
- are under medical supervision for diabetes or have multiple sclerosis (MS), rheumatoid arthritis (RA) or an auto-immune condition

Sore Throat Warning

Severe or persistent sore throat or sore throat accompanied by high fever, headache, nausea, and vomiting may be serious. Consult physician promptly.

Do not use

- if taking loperamide
- while operating a motor vehicle or machinery or consuming alcohol

Stop use and ask your healthcare practitioner if symptoms persist for more than 7 days or are accompanied by fever, rash or persistent headache

Cold-EEZE® Plus Nighttime Multi-Symptom Relief Cold & Flu QuickMelts® is a combination product formulated to help you to sleep easier, reduce the duration of the common cold and to help for temporary relief of cold and flu symptoms. It is insufficient treatment for Influenza or Allergies.

PREGNANCY OR BREAST FEEDING

If pregnant or breastfeeding, ask a healthcare practitioner before use.

Keep out of reach of children. In case of overdose, get medical help or contact a poison control center right away.

Directions

- Take Cold-EEZE® Plus Nighttime Multi-Symptom Relief Cold & Flu QuickMelts® at night when you have cold or flu symptoms
- Adults:
  - Dissolve entire tablet in mouth. Do not chew. Do not swallow whole.
  - Take 1 tablet 1 hour before bedtime
  - Do not eat or drink for 15 minutes after use, otherwise, drink plenty of fluids
- Recommended dose is 1 tablet for adults
- Allow 6-8 hours for sleep after taking tablet
- For individuals under the age of 18, consult a healthcare practitioner before use

Other information

- Do not take Cold-EEZE® Plus Nighttime Multi-Symptom Relief Cold & Flu QuickMelts® on an empty stomach to avoid possible minor stomach upset
- Store in a cool and dry place

Inactive ingredients

crospovidone, glycine, magnesium stearate, malic acid, maltodextrin, mannitol, microcrystalline cellulose, natural color from carrot and hibiscus concentrates, natural flavors, natural menthol flavor, polyethylene glycol, silicon dioxide, sodium lauryl sulfate, sodium starch glycolate, stevia, sucralose

Questions or Comments
Call 1-800-505-2653
(M-F: 9AM-5PM EST)

Distributed by:
ProPhase Labs, Inc.
P.O. Box 1349, Doylestown
PA 18901

PRINCIPAL DISPLAY PANEL - 18 Tablet Blister Pack Carton

Relax & Sleep!^+
#1 Pharmacist Recommended

Cold-EEZE®

ZINC GLUCONATE GLYCINE

SHORTENS YOUR COLD,
WORKS FASTER®+

Plus Nighttime
Multi-Symptom Relief
Cold & Flu

ALSO HELPS RELIEVE:

☑ Cough^+
☑ Sore Throat^+
☑ Chest Congestion^+

Fall asleep faster,
naturally^+

CLINICALLY PROVEN
INGREDIENT

18
QuickMelts®
HOMEOPATHIC
(actual
size)

NATURAL FLAVOR
Mixed Berry